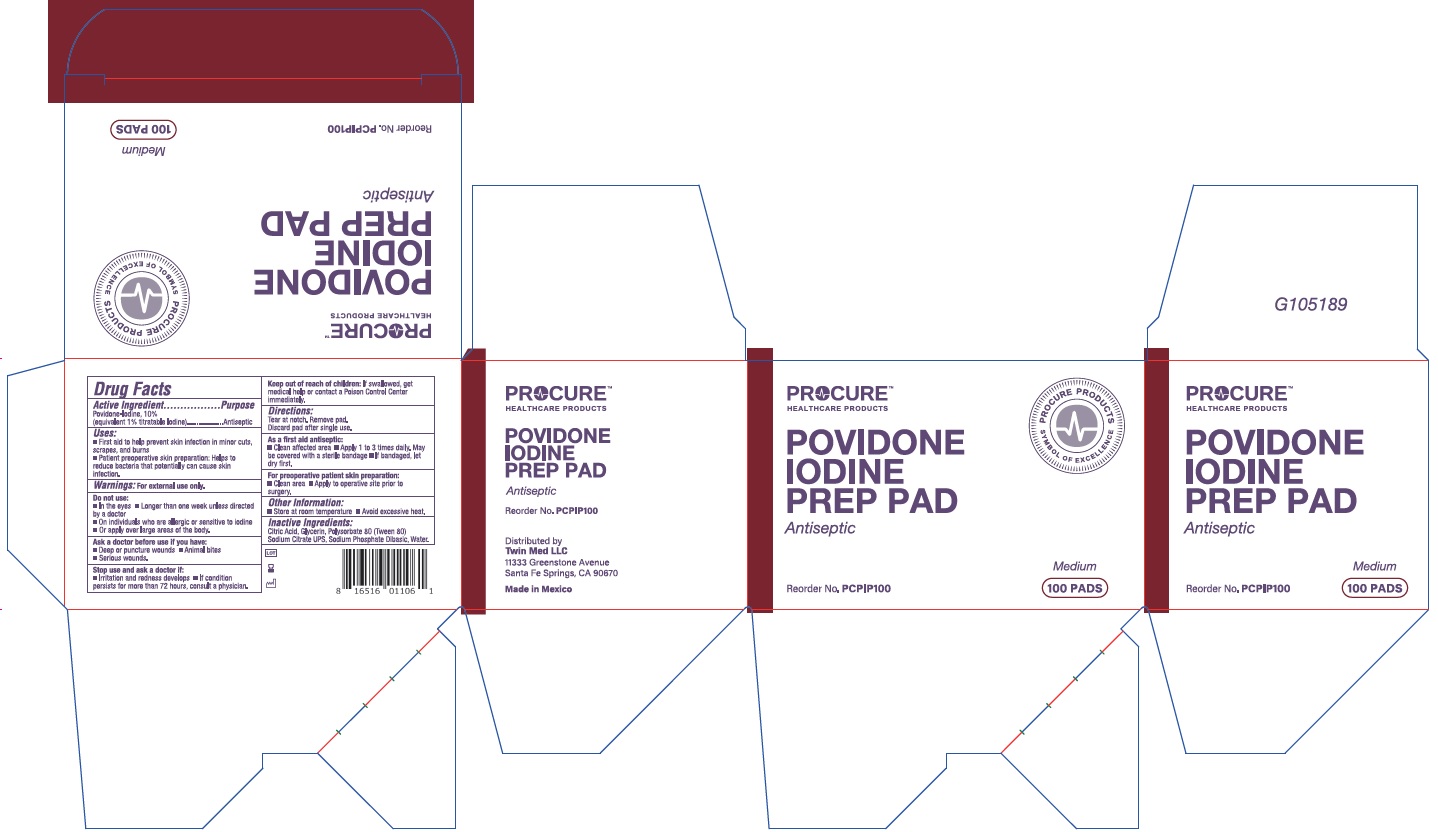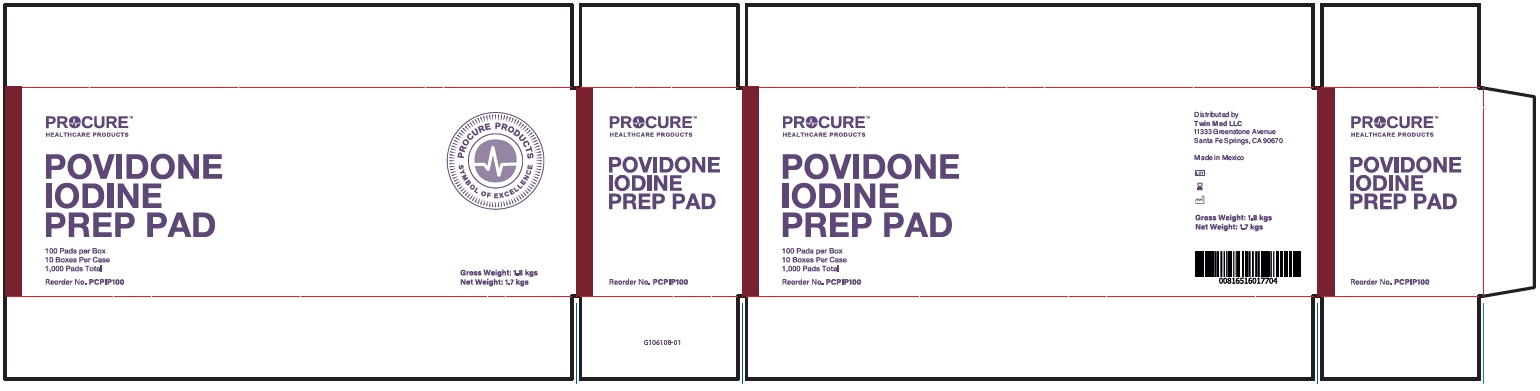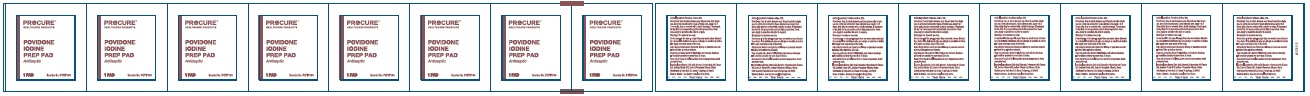 DRUG LABEL: Povidone Iodine
NDC: 55681-751 | Form: SWAB
Manufacturer: TwinMed LLC
Category: otc | Type: HUMAN OTC DRUG LABEL
Date: 20251218

ACTIVE INGREDIENTS: POVIDONE-IODINE 0.1 g/1 g
INACTIVE INGREDIENTS: SODIUM CITRATE; SODIUM PHOSPHATE, DIBASIC, ANHYDROUS; CITRIC ACID MONOHYDRATE; WATER; POLYSORBATE 80; GLYCERIN

Povidone Iodine Prep Pad

Active Ingredient

Povidone Iodine 10%

Purpose

Antiseptic

Uses:

- First aid to help prevent skin infection in minor cuts, scrapes, and burns
- Patient preoperative skin preparation: Helps to reduce bacteria that potentially can cause skin infection.

Warnings:

For external use only.

Do not use:

- In the eyes
- Longer than one week unless directed by a doctor
- On individuals who are allergic or sensitive to iodine
- Or apply over large areas of the body

Ask a doctor before use if you have:

- Deep or puncture wounds
- Animal bites
- Serious wounds

Stop use and ask a doctor if:

- Irritation and redness develops
- If condition persists for more than 72 hours, consult a physician.

Keep out of reach of children:

If swallowed, get medical help or contact a Poison Control Center immediately.

Directions:

Tear at notch. Remove applicator. Discard applicator after single use.

As a first aid antispetic:

- Clean affected area
- Apply 1-3 times daily
- May be covered with a sterile bandage
- If bandaged, let dry first.

For preoperative patient skin preparation

- Clean area
- Apply to operative site prior to surgery using applicator.

Other Information:

- Store at room temperature
- Avoid excessive heat

Inactive Ingredients

Citric Acid, Glycerin, Polysorbate 80 (Tween 80), Sodium Citrate UPS, Sodium Phosphate Dibasic, Water

Principal Display Panel

PROCURE

HEALTHCARE PRODUCTS

POVIDONE

IODINE

PREP PAD

Antiseptic

100 PADS